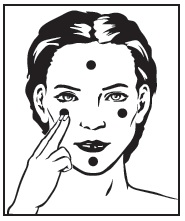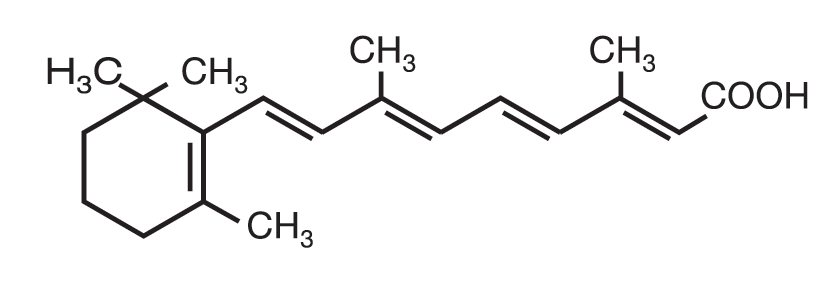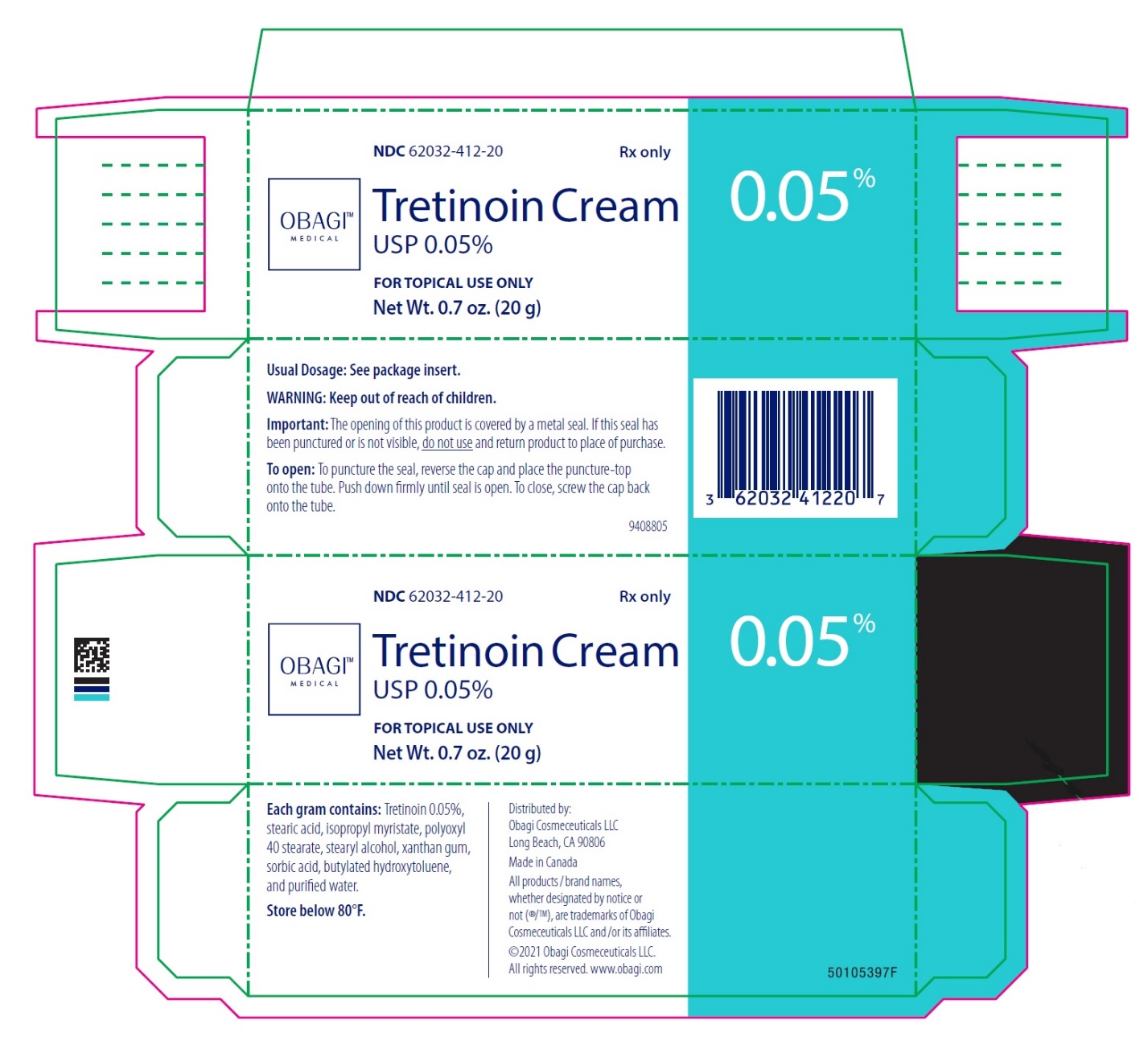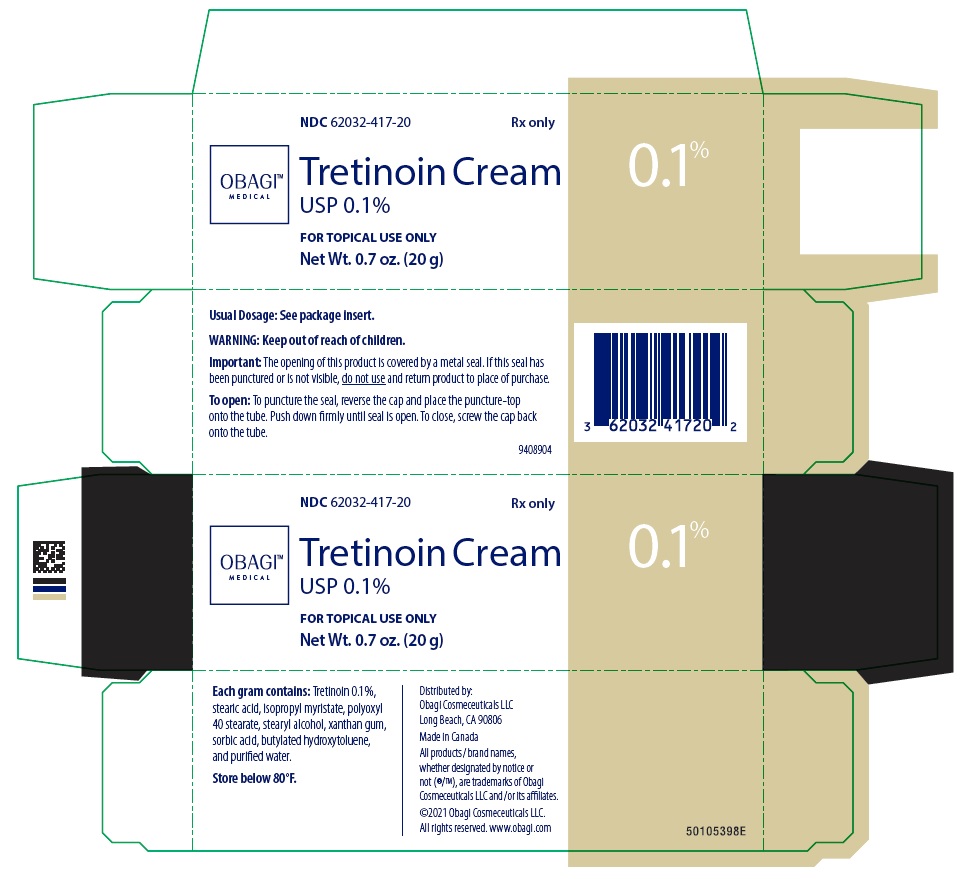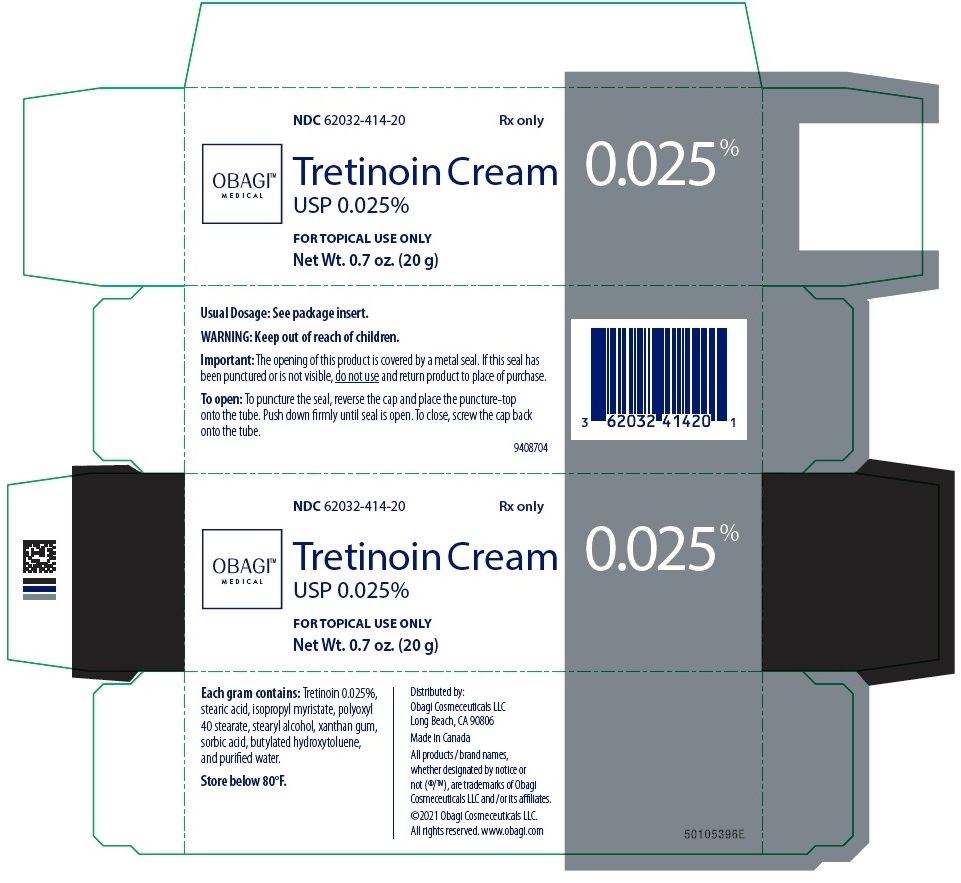 DRUG LABEL: Tretinoin Cream
NDC: 62032-417 | Form: CREAM
Manufacturer: Obagi Cosmeceuticals LLC
Category: prescription | Type: HUMAN PRESCRIPTION DRUG LABEL
Date: 20250211

ACTIVE INGREDIENTS: TRETINOIN 1 mg/1 g
INACTIVE INGREDIENTS: STEARIC ACID; ISOPROPYL MYRISTATE; STEARYL ALCOHOL; POLYOXYL 40 STEARATE; XANTHAN GUM; SORBIC ACID; BUTYLATED HYDROXYTOLUENE; WATER

TRETINOIN CREAM

DESCRIPTION

Tretinoin Cream is used for the topical treatment of acne vulgaris. Tretinoin Cream contains tretinoin in one of three strengths, 0.1%, 0.05%, or 0.025% by weight, in a hydrophilic cream vehicle of stearic acid, isopropyl myristate, polyoxyl 40 stearate, stearyl alcohol, xanthan gum, sorbic acid, butylated hydroxytoluene, and purified water. Chemically, tretinoin is all-trans-retinoic acid and has the following structure:

CLINICAL PHARMACOLOGY

Although the exact mode of action of tretinoin is unknown, current evidence suggests that topical tretinoin decreases cohesiveness of follicular epithelial cells with decreased microcomedo formation. Additionally, tretinoin stimulates mitotic activity and increased turnover of follicular epithelial cells causing extrusion of the comedones.

INDICATIONS AND USAGE

Tretinoin is indicated for topical application in the treatment of acne vulgaris. The safety and efficacy of the long-term use of this product in the treatment of other disorders have not been established.

CONTRAINDICATIONS

Use of the product should be discontinued if hypersensitivity to any of the ingredients is noted.

PRECAUTIONS

General

If a reaction suggesting sensitivity or chemical irritation occurs, use of the medication should be discontinued. Exposure to sunlight, including sunlamps, should be minimized during the use of tretinoin, and patients with sunburn should be advised not to use the product until fully recovered because of heightened susceptibility to sunlight as a result of the use of tretinoin. Patients who may be required to have considerable sun exposure due to occupation and those with inherent sensitivity to the sun should exercise particular caution. Use of sunscreen products and protective clothing over treated areas is recommended when exposure cannot be avoided. Weather extremes, such as wind or cold, also may be irritating to patients under treatment with tretinoin.

Tretinoin acne treatment should be kept away from the eyes, the mouth, angles of the nose, and mucous membranes. Topical use may induce severe local erythema and peeling at the site of application. If the degree of local irritation warrants, patients should be directed to use the medication less frequently, discontinue use temporarily, or discontinue use altogether. Tretinoin has been reported to cause severe irritation on eczematous skin and should be used with utmost caution in patients with this condition.

Drug Interactions

Concomitant topical medication, medicated or abrasive soaps and cleansers, soaps and cosmetics that have a strong drying effect, and products with high concentrations of alcohol, astringents, spices or lime should be used with caution because of possible interaction with tretinoin. Particular caution should be exercised in using preparations containing sulfur, resorcinol, or salicylic acid with tretinoin. It also is advisable to “rest” a patient’s skin until the effects of such preparations subside before use of tretinoin is begun.

Carcinogenesis, Mutagenesis, Impairment to Fertility

In a 91-week dermal study in which CD-1 mice were administered 0.017% and 0.035% formulations of tretinoin, cutaneous squamous cell carcinomas and papillomas in the treatment area were observed in some female mice. A dose-related incidence of liver tumors in male mice was observed at those same doses. The maximum systemic doses associated with the administered 0.017% and 0.035% formulations are 0.5 and 1.0 mg/kg/day, respectively. These doses are two and four times the maximum human systemic dose, when adjusted for total body surface area. The biological significance of these findings is not clear because they occurred at doses that exceeded the dermal maximally tolerated dose (MTD) of tretinoin and because they were within the background natural occurrence rate for these tumors in this strain of mice. There was no evidence of carcinogenic potential when 0.025 mg/kg/day of tretinoin was administered topically to mice (0.1 times the maximum human systemic dose, adjusted for total body surface area). For purposes of comparisons of the animal exposure to systemic human exposure, the maximum human systemic dose is defined as 1 gram of 0.1% RETIN-A applied daily to a 50 kg person (0.02 mg tretinoin/kg body weight).

Studies in hairless albino mice suggest that concurrent exposure to tretinoin may enhance the tumorigenic potential of carcinogenic doses of UVB and UVA light from a solar simulator. This effect has been confirmed in a later study in pigmented mice, and dark pigmentation did not overcome the enhancement of photocarcinogenesis by 0.05% tretinoin. Although the significance of these studies to humans is not clear, patients should minimize exposure to sunlight or artificial ultraviolet irradiation sources.

The mutagenic potential of tretinoin was evaluated in the Ames assay and in the in vivo mouse micronucleus assay, both of which were negative.

In dermal Segment I fertility studies of another tretinoin formulation in rats, slight (not statistically significant) decreases in sperm count and motility were seen at 0.5 mg/kg/day (4 times the maximum human systemic dose adjusted for total body surface area) and slight (not statistically significant) increases in the number and percent of nonviable embryos in females treated with 0.25 mg/kg/day (2 times the maximum human systemic dose adjusted for total body surface area) and above were observed. A dermal Segment III study with RETIN-A has not been performed in any species. In oral Segment I and Segment III studies in rats with tretinoin, decreased survival of neonates and growth retardation were observed at doses in excess of 2 mg/kg/day (16 times the human topical dose adjusted for total body surface area).

Pregnancy Teratogenic Effects

Oral tretinoin has been shown to be teratogenic in rats, mice, hamsters, and subhuman primates. It was teratogenic and fetotoxic in Wistar rats when given orally or topically in doses greater than 1 mg/kg/day (8 times the maximum human systemic dose adjusted for total body surface area). However, variations in teratogenic doses among various strains of rats have been reported. In the cynomolgus monkey, which metabolically is closer to humans for tretinoin than the other species examined, fetal malformations were reported at doses of 10 mg/kg/day or greater, but none were observed at 5 mg/kg/day (83 times the maximum human systemic dose adjusted for total body surface area), although increased skeletal variations were observed at all doses. A dose-related increase in embryolethality and abortion was reported. Similar results have also been reported in pigtail macaques.

Topical tretinoin in animal teratogenicity tests has generated equivocal results. There is evidence for teratogenicity (shortened or kinked tail) of topical tretinoin in Wistar rats at doses greater than 1 mg/kg/day (8 times the maximum human systemic dose adjusted for total body surface area). Anomalies (humerus: short 13%, bent 6%, os parietale incompletely ossified 14%) have also been reported when 10 mg/kg/day was topically applied.

There are other reports in New Zealand White rabbits administered doses of greater than 0.2 mg/kg/day (3.3 times the maximum human systemic dose adjusted for total body surface area) of an increased incidence of domed head and hydrocephaly, typical of retinoid-induced fetal malformations in this species.

In contrast, several well-controlled animal studies have shown that dermally applied tretinoin may be fetotoxic, but not overly teratogenic in rats and rabbits at doses of 1.0 and 0.5 mg/kg/day, respectively (8 times the maximum human systemic dose adjusted for total body surface area in both species).

With widespread use of any drug, a small number of birth defect reports associated temporally with the administration of the drug would be expected by chance alone. Thirty human cases of temporally associated congenital malformations have been reported during two decades of clinical use of RETIN-A. Although no definite pattern of teratogenicity and no causal association have been established from these cases, five of the reports describe the rare birth defect category holoprosencephaly (defects associated with incomplete midline development of the forebrain). The significance of these spontaneous reports in terms of risk to the fetus is not known.

Nonteratogenic Effects

Topical tretinoin has been shown to be fetotoxic in rabbits when administered 0.5 mg/kg/day (8 times the maximum human systemic dose adjusted for total body surface area). Oral tretinoin has been shown to be fetotoxic, resulting in skeletal variations and increased intrauterine death in rats when administered 2.5 mg/kg/day (20 times the maximum human systemic dose adjusted for total body surface area).
There are, however, no adequate and well-controlled studies in pregnant women. Tretinoin should be used during pregnancy only if the potential benefit justifies the potential risk to the fetus.

Nursing Mothers

It is not known whether this drug is excreted in human milk. Because many drugs are excreted in human milk, caution should be exercised when tretinoin is administered to a nursing woman.
Pediatric Use
Safety and effectiveness in pediatric patients below the age of 12 have not been established.

Geriatric Use
Safety and effectiveness in a geriatric population have not been established. Clinical studies of RETIN-A did not include sufficient numbers of subjects aged 65 and over to determine whether they respond differently from younger patients.

ADVERSE REACTIONS

The skin of certain sensitive individuals may become excessively red, edematous, blistered, or crusted. If these effects occur, the medication should either be discontinued until the integrity of the skin is restored, or the medication should be adjusted to a level the patient can tolerate. True contact allergy to topical tretinoin is rarely encountered. Temporary hyper- or hypopigmentation has been reported with repeated application of tretinoin. Some individuals have been reported to have heightened susceptibility to sunlight while under treatment with tretinoin. To date, all adverse effects of tretinoin have been reversible upon discontinuance of therapy (see DOSAGE AND ADMINISTRATION).

To report SUSPECTED ADVERSE REACTIONS, contact Obagi Cosmeceuticals LLC at 1-800-636-7546 or FDA at 1-800-FDA-1088 or www.fda.gov/medwatch.

OVERDOSAGE

If medication is applied excessively, no more rapid or better results will be obtained and marked redness, peeling, or discomfort may occur. Oral ingestion of the drug may lead to the same side effects as those associated with excessive oral intake of Vitamin A.

DOSAGE AND ADMINISTRATION

Tretinoin Cream should be applied once a day, before retiring, to the skin where acne lesions appear, using enough to cover the entire affected area lightly.

Application may cause a transitory feeling of warmth or slight stinging. In cases where it has been necessary to temporarily discontinue therapy or to reduce the frequency of application, therapy may be resumed or frequency of application increased when the patients become able to tolerate the treatment.

Alterations of vehicle, drug concentration, or dose frequency should be closely monitored by careful observation of the clinical therapeutic response and skin tolerance.

During the early weeks of therapy, an apparent exacerbation of inflammatory lesions may occur. This is due to the action of the medication on deep, previously unseen lesions and should not be considered a reason to discontinue therapy.

Therapeutic results should be noticed after 2 to 3 weeks but more than 6 weeks of therapy may be required before definite beneficial effects are seen.

Once the acne lesions have responded satisfactorily, it may be possible to maintain the improvement with less frequent applications, or other dosage forms.

Patients treated with tretinoin acne treatment may use cosmetics, but the area to be treated should be cleansed thoroughly before the medication is applied (see PRECAUTIONS).

HOW SUPPLIED

Tretinoin is supplied as:

Tretinoin Cream

NDC Code | Strength | Quantity
62032-414-20 | 0.025% Cream | 20 g
62032-412-20 | 0.05% Cream | 20 g
62032-417-20 | 0.1% Cream | 20 g

Storage Conditions:

Tretinoin Cream, 0.1%, 0.05%, and 0.025%: store below 80°F.

Distributed by:
Obagi Cosmeceuticals LLC
Long Beach, CA 90806

All products/brand names, whether designated by notice or not (®/TM), are trademarks of Obagi Cosmeceuticals LLC and/or its affiliates.

©2021 Obagi Cosmeceuticals LLC.

All rights reserved.

www.obagi.com

Rev. 01/2021

9441004

PATIENT INSTRUCTIONS TRETINOIN CREAM For Topical Use Only Acne Treatment IMPORTANT Read Directions Carefully Before Using

THIS LEAFLET TELLS YOU ABOUT TRETINOIN ACNE TREATMENT AS PRESCRIBED BY YOUR PHYSICIAN. THIS PRODUCT IS TO BE USED ONLY ACCORDING TO YOUR DOCTOR’S INSTRUCTIONS, AND IT SHOULD NOT BE APPLIED TO OTHER AREAS OF THE BODY OR TO OTHER GROWTHS OR LESIONS. THE LONG-TERM SAFETY AND EFFECTIVENESS OF THIS PRODUCT IN OTHER DISORDERS HAVE NOT BEEN EVALUATED. IF YOU HAVE ANY QUESTIONS, BE SURE TO ASK YOUR DOCTOR.

PRECAUTIONS

The effects of the sun on your skin. As you know, overexposure to natural sunlight or the artificial sunlight of a sunlamp can cause sunburn. Overexposure to the sun over many years may cause premature aging of the skin and even skin cancer. The chance of these effects occurring will vary depending on skin type, the climate and the care taken to avoid overexposure to the sun. Therapy with Tretinoin Cream may make your skin more susceptible to sunburn and other adverse effects of the sun, so unprotected exposure to natural or artificial sunlight should be minimized.

Laboratory findings. When laboratory mice are exposed to artificial sunlight, they often develop skin tumors. These sunlight-induced tumors may appear more quickly and in greater number if the mouse is also topically treated with the active ingredient in Tretinoin Cream, tretinoin. In some studies, under different conditions, however, when mice treated with tretinoin were exposed to artificial sunlight, the incidence and rate of development of skin tumors was reduced. There is no evidence to date that tretinoin alone will cause the development of skin tumors in either laboratory animals or humans. However, investigations in this area are continuing.

Use caution in the sun. When outside, even on hazy days, areas treated with Tretinoin Cream should be protected. An effective sunscreen should be used any time you are outside (consult your physician for a recommendation of an SPF level which will provide you with the necessary high level of protection). For extended sun exposure, protective clothing, like a hat, should be worn. Do not use artificial sunlamps while you are using Tretinoin Cream. If you do become sunburned, stop your therapy with Tretinoin Cream until your skin has recovered.

Avoid excessive exposure to wind or cold. Extremes of climate tend to dry or burn normal skin. Skin treated with Tretinoin Cream may be more vulnerable to these extremes. Your physician can recommend ways to manage your acne treatment under such conditions.

Possible problems. The skin of certain sensitive individuals may become excessively red, swollen, blistered or crusted. If you are experiencing severe or persistent irritation, discontinue the use of Tretinoin Cream and consult your physician.
There have been reports that, in some patients, areas treated with Tretinoin Cream developed a temporary increase or decrease in the amount of skin pigment (color) present. The pigment in these areas returned to normal either when the skin was allowed to adjust to Tretinoin Cream or therapy was discontinued.

Use other medications only on your physician’s advice. Only your physician knows which other medications may be helpful during treatment and will recommend them to you if necessary. Follow the physician’s instructions carefully. In addition, you should avoid preparations that may dry or irritate your skin. These preparations may include certain astringents, toiletries containing alcohol, spices or lime, or certain medicated soaps, shampoos and hair permanent solutions. Do not allow anyone else to use this medication.

Do not use other medications with Tretinoin Cream which are not recommended by your doctor. The medications you have used in the past might cause unnecessary redness or peeling.

If you are pregnant, think you are pregnant or are nursing an infant: No studies have been conducted in humans to establish the safety of Tretinoin Cream in pregnant women. If you are pregnant, think you are pregnant, or are nursing a baby, consult your physician before using this medication.

AND WHILE YOU’RE ON TRETINOIN CREAM THERAPY

Use a mild, non-medicated soap. Avoid frequent washings and harsh scrubbing. Acne isn’t caused by dirt, so no matter how hard you scrub, you can’t wash it away. Washing too frequently or scrubbing too roughly may at times actually make your acne worse.

Wash your skin gently with a mild, bland soap. Two or three times a day should be sufficient. Pat skin dry with a towel. Let the face dry 20 to 30 minutes before applying Tretinoin Cream. Remember, excessive irritation such as rubbing, too much washing, use of other medications not suggested by your physician, etc., may worsen your acne.

HOW TO USE TRETINOIN CREAM

To get the best results with Tretinoin Cream therapy, it is necessary to use it properly. Forget about the instructions given for other products and the advice of friends. Just stick to the special plan your doctor has laid out for you and be patient. Remember, when Tretinoin Cream is used properly, many users see improvement by 12 weeks. AGAIN, FOLLOW INSTRUCTIONS – BE PATIENT – DON’T START AND STOP THERAPY ON YOUR OWN – IF YOU HAVE QUESTIONS, ASK YOUR DOCTOR.

To help you use the medication correctly, keep these simple instructions in mind.

- Apply Tretinoin Cream once daily before bedtime, or as directed by your physician. Your physician may advise, especially if your skin is sensitive, that you start your therapy by applying Tretinoin Cream every other night. First, wash with a mild soap and dry your skin gently. WAIT 20 TO 30 MINUTES BEFORE APPLYING MEDICATION;it is important for skin to be completely dry in order to minimize possible irritation.
- It is better not to use more than the amount suggested by your physician or to apply more frequently than instructed. Too much may irritate the skin, waste medication and won’t give faster or better results.
- Keep the medication away from the corners of the nose, mouth, eyes and open wounds. Spread away from these areas when applying.
- Cream: Squeeze about a half inch or less of medication onto the fingertip. While that should be enough for your whole face, after you have some experience with the medication, you may find you need slightly more or less to do the job. The medication should become invisible almost immediately. If it is still visible, you are using too much. Cover the affected area lightly with Tretinoin Cream by first dabbing it on your forehead, chin and both cheeks, then spreading it over the entire affected area. Smooth gently into the skin.
- It is recommended that you apply a moisturizer or a moisturizer with sunscreen that will not aggravate your acne (noncomedogenic) every morning after you wash.

WHAT TO EXPECT WITH YOUR NEW TREATMENT

Tretinoin Cream works deep inside your skin and this takes time. You cannot make Tretinoin Cream work any faster by applying more than one dose each day, but an excess amount of Tretinoin Cream may irritate your skin. Be patient.

There may be some discomfort or peeling during the early days of treatment. Some patients also notice that their skin begins to take on a blush.

These reactions do not happen to everyone. If they do, it is just your skin adjusting to Tretinoin Cream and this usually subsides within 2 to 4 weeks. These reactions can usually be minimized by following instructions carefully. Should the effects become excessively troublesome, consult your doctor.

BY 3 TO 6 WEEKS, some patients notice an appearance of new blemishes (papules and pustules). At this stage it is important to continue using Tretinoin Cream.

If Tretinoin Cream is going to have a beneficial effect for you, you should notice a continued improvement in your appearance after 6 to 12 weeks of therapy. Don’t be discouraged if you see no immediate improvement. Don’t stop treatment at the first signs of improvement.

Once your acne is under control you should continue regular application of Tretinoin Cream until your physician instructs otherwise.

IF YOU HAVE QUESTIONS

All questions of a medical nature should be taken up with your doctor. For more information about Tretinoin Cream, call our toll-free number: 1-800-636-7546.

Storage Conditions: Tretinoin Cream, 0.1%, 0.05%, and 0.025%: store below 80°F.

Distributed by:
Obagi Cosmeceuticals LLC
Long Beach, CA 90806

All products/brand names, whether designated by notice or not (®/TM), are trademarks of Obagi Cosmeceuticals LLC and/or its affiliates.

©2021 Obagi Cosmeceuticals LLC.

All rights reserved.

www.obagi.com

Rev. 01/2021

9441004

PACKAGE/LABEL PRINCIPAL DISPLAY PANEL - Tretinoin Cream 0.1%

NDC 62032-417-20

Rx only

OBAGI™
MEDICAL

Tretinoin Cream 0.1%
USP 0.1%

FOR TOPICAL USE ONLY

Net Wt. 0.7 oz. (20 g)

PACKAGE/LABEL PRINCIPAL DISPLAY PANEL -Tretinoin Cream 0.05%

NDC 62032-412-20

Rx only

OBAGI™
MEDICAL

Tretinoin Cream 0.05%
USP 0.05%

FOR TOPICAL USE ONLY

Net Wt. 0.7 oz. (20 g)

PRINCIPAL DISPLAY PANEL - Tretinoin Cream 0.025%

NDC 62032-414-20

Rx only

OBAGI™
MEDICAL

Tretinoin Cream 0.025%
USP 0.025%

FOR TOPICAL USE ONLY

Net Wt. 0.7 oz. (20 g)